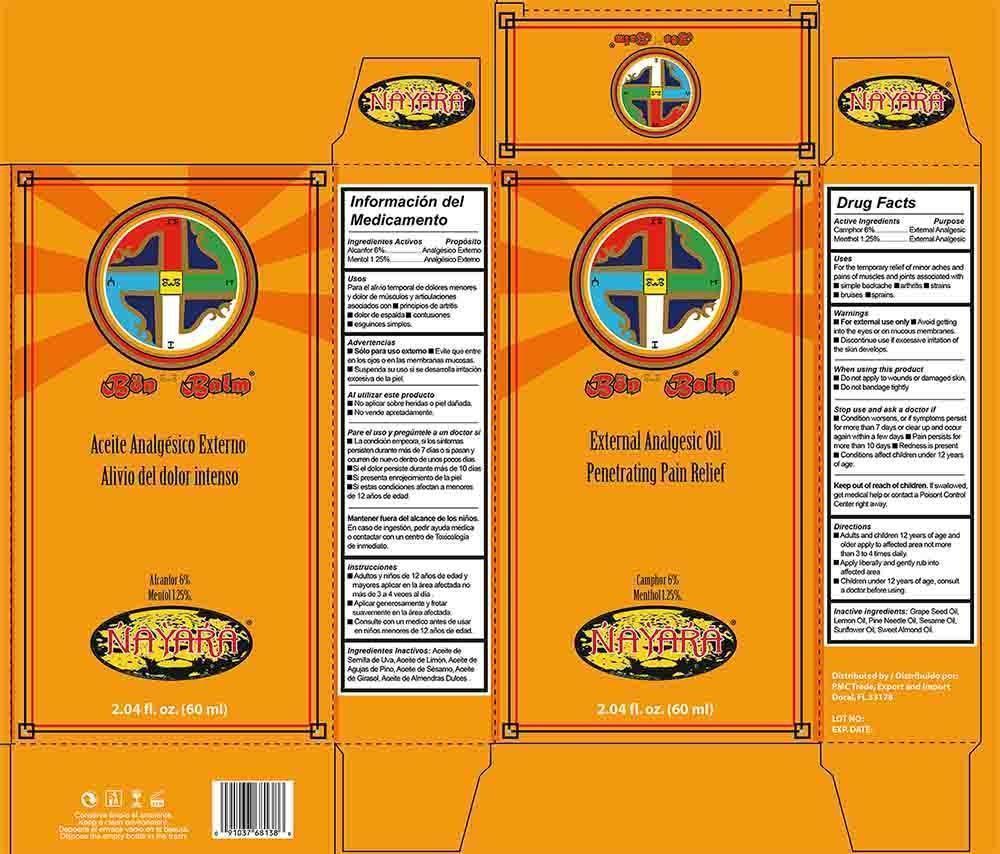 DRUG LABEL: Bon Balm
NDC: 68973-001 | Form: OIL
Manufacturer: PMC TRADE, EXPORT AND IMPORT
Category: otc | Type: HUMAN OTC DRUG LABEL
Date: 20140627

ACTIVE INGREDIENTS: CAMPHOR (SYNTHETIC) 6 g/100 mL; MENTHOL 1.25 g/100 mL
INACTIVE INGREDIENTS: GRAPE SEED OIL; LEMON OIL; PINE NEEDLE OIL (PINUS SYLVESTRIS); SESAME OIL; SUNFLOWER OIL; ALMOND OIL

Drug Facts

Active Ingredients

Camphor 6%

Menthol 1.25%

Purpose

External Analgesic

External Analgesic

Uses

For the temporary relief of minor aches and pains of muscles and joints associated with

■ simple backache ■ arthritis ■ strains ■ bruises ■ sprains

Warnings

■ For external use only ■ Avoid getting into the eyes or on mucous membranes

■ Discontinue use if excessive irritation of the skin develops

When using this product

■ Do not apply to wound or damaged skin.

■ Do not bandage tightly

Stop use and ask a doctor if

■ Condition worsens, or if symptoms persist for more than 7 days or clear up and occur again within a few days

■ Pain persists for more than 10 days conditions

■ Redness is present

■ Conditions affect children under 12 years of age

Keep out of reach of children

If swallowed, get medical help or contact a poison control center right away

Directions

■ Adults and children 12 years of age and older apply to affected area not more than 3 to 4 time daily

■ Apply liberally and gently rub into affected area

■ Children under 12 years of age, consult a doctor before using

Inactive ingredients

Grape Seed Oil, Lemon Oil, Pine Needle Oil, Sesame Oil, Sunflower Oil, Sweet Almond Oil